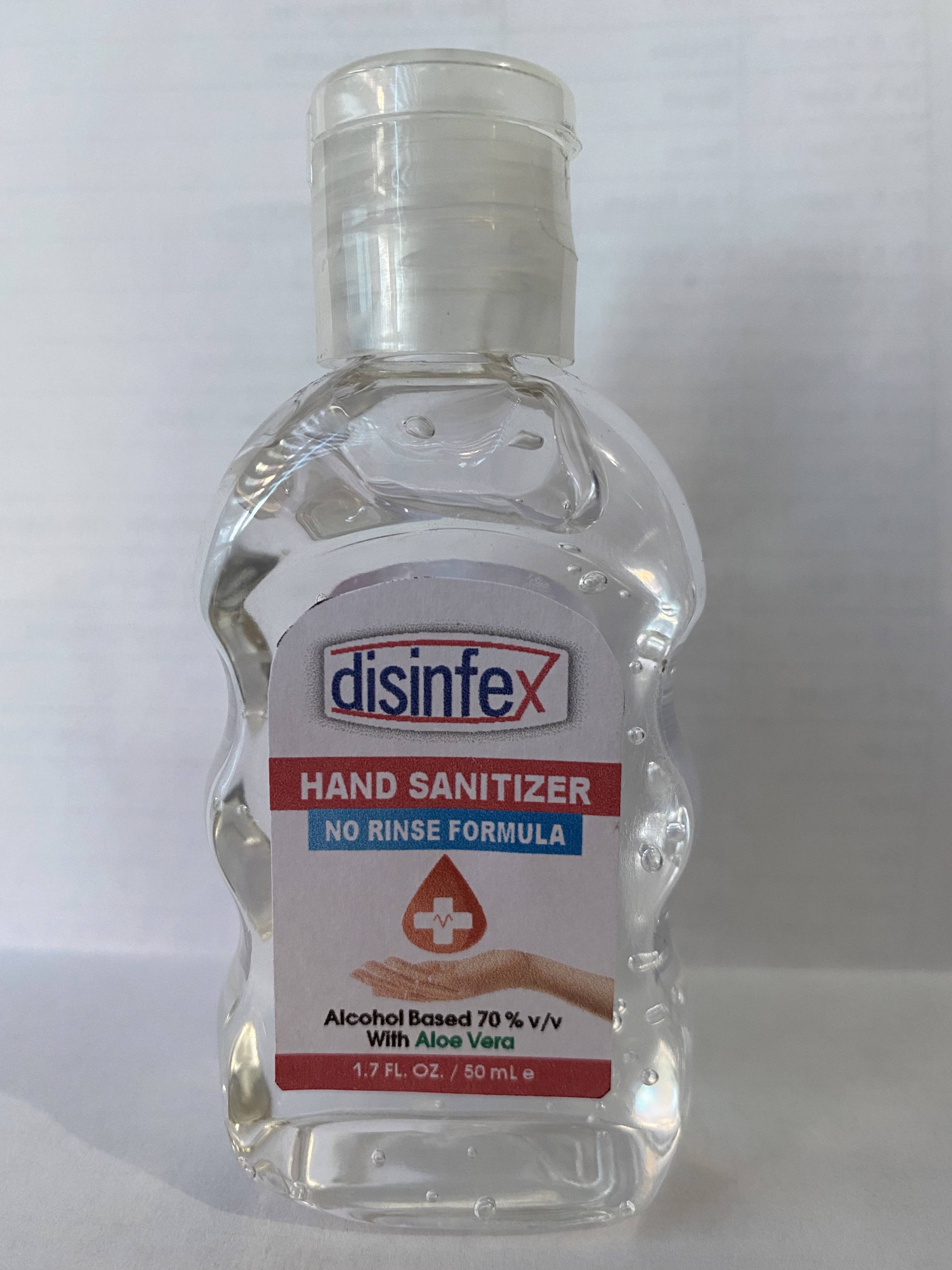 DRUG LABEL: DISINFEX
NDC: 79320-120 | Form: GEL
Manufacturer: RK KOZMETIK VE HIJYEN URUNLERI SANAYI DIS TICARET ANONIM SIRKETI
Category: otc | Type: HUMAN OTC DRUG LABEL
Date: 20200722

ACTIVE INGREDIENTS: ALCOHOL 70 mL/100 mL
INACTIVE INGREDIENTS: GLYCERIN 0.5 mL/100 mL; CARBOMER 940 0.3 mL/100 mL; WATER; ALOE VERA LEAF 0.1 mL/100 mL; AMINOMETHYLPROPANOL 0.15 mL/100 mL

This is a hand sanitizer manufactured according to the Temporary Policy for Preparation of Certain Alcohol-Based Hand Sanitizer Products During the Public Health Emergency (CoViD-19); Guidance for Industry.

The hand sanitizer is manufactured using only the following United States Pharmacopoeia (USP) grade ingredients in the preparation of the product (percentage in final product formulation) consistent with) recommendations:

1. Alcohol (ethanol) (USP or Food Chemical Codex (FCC) grade) (70%, volume/volume (v/v)) in an aqueous solution denatured according to Alcohol and Tobacco Tax and Trade Bureau regulations in 27 CFR part 20.
2. Glycerol (0.5% v/v).
3. Aloe Vera Leaf (0.1% v/v).
4. Carbomer 940 (0.3% v/v).
5. Aminomethylpropanol (0.15% v/v).
6. Sterile distilled water

The firm does not add other active or inactive ingredients. Different or additional ingredients may impact the quality and potency of the product.

Active Ingredient(s)

Alcohol 70% v/v. Purpose: Antiseptic

Purpose

Antiseptic, Disinfex Hand Sanitizer

Uses

to help reduce bacteria on the skin. For use when soap and water are not avaliable.

Warnings

For external use only. Flammable liquid and vapor. Keep away from heat/sparks/open flame. No smoking. Avoid sprayin in eyes.

When using this product avoid contact with eyes. If contact occurs, rinse thoroughly with water.

Stop use and ask a doctor if irritation or redness devolops and lasts.

Keep out of reach of children. In case of accidental ingestion, get medical help or contact a poison Control Center immediately.

Directions

- Put enough product in your palm to cover hands and rub hands together until dry.
- Children under 6 years should be supervised when using this product.

Other information

- Store between 15-30C (59-86F). Avoid freezing and excessive heat above 40C (104F)
- may discolor certain fabrics or surfaces.

Inactive ingredients

Water (Aqua), Glycerin, Aloe Barbadensis Leaf Juice, Carbomer, Aminomethylpropanol.

Package Label - Principal Display Panel

50 mL NDC: 79320-120-01